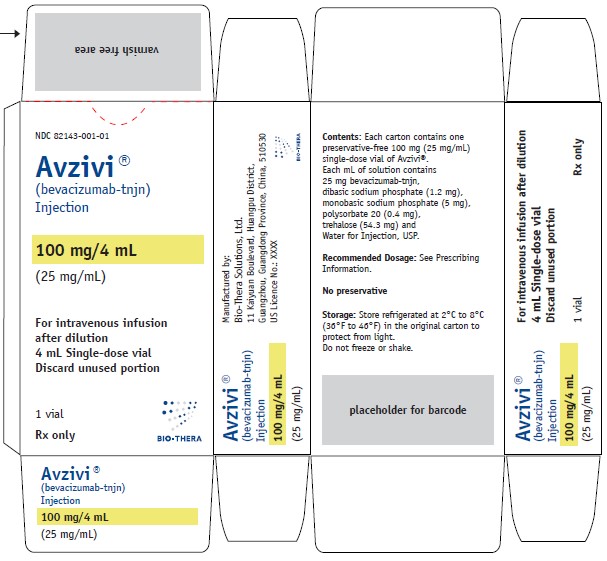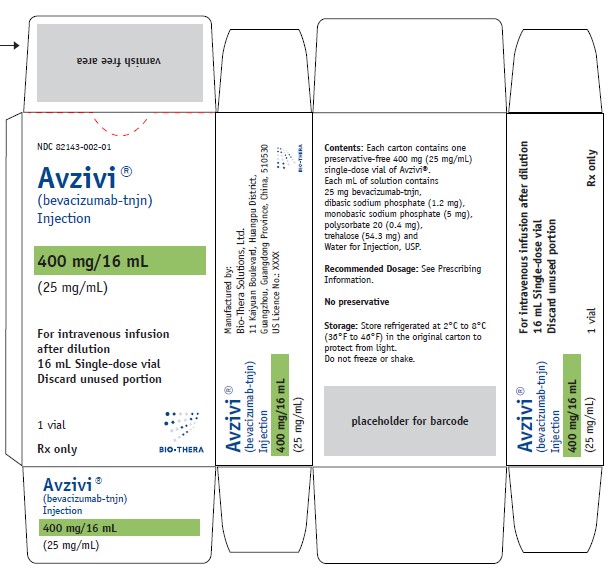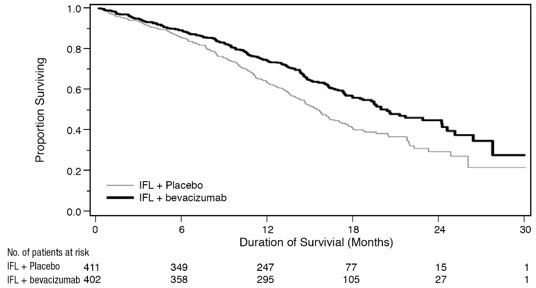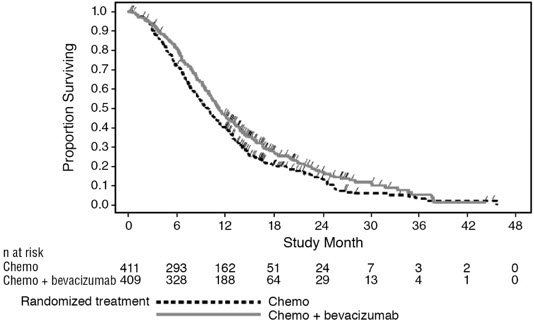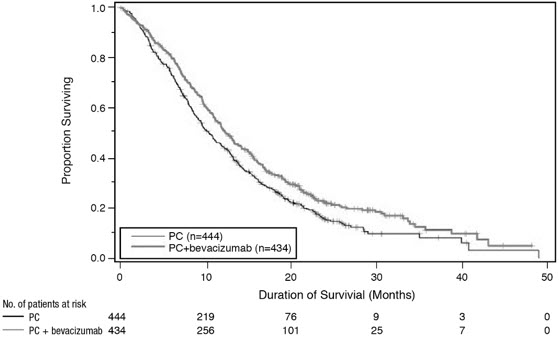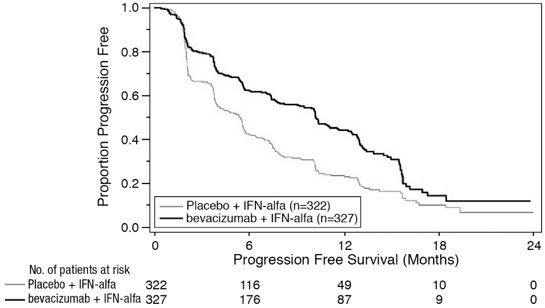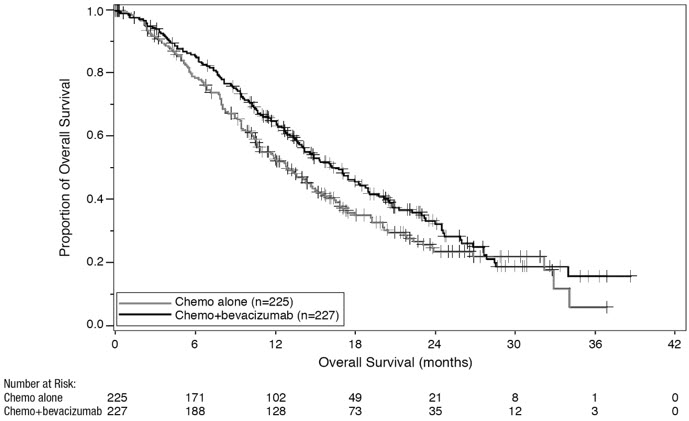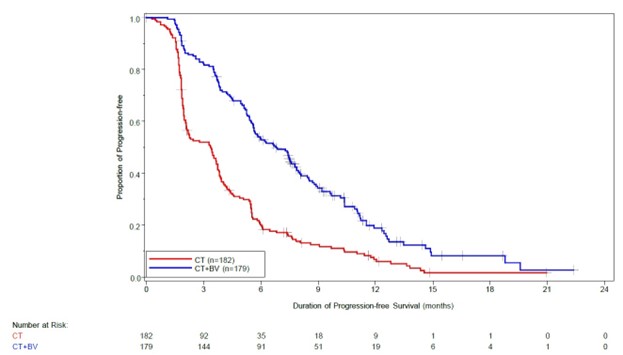 DRUG LABEL: Avzivi
NDC: 82143-001 | Form: INJECTION, SOLUTION
Manufacturer: Bio-Thera Solutions, Ltd.
Category: prescription | Type: HUMAN PRESCRIPTION DRUG LABEL
Date: 20250930

ACTIVE INGREDIENTS: BEVACIZUMAB-TNJN 100 mg/4 mL
INACTIVE INGREDIENTS: TREHALOSE DIHYDRATE 240 mg/4 mL; SODIUM PHOSPHATE, DIBASIC, ANHYDROUS 4.8 mg/4 mL; SODIUM PHOSPHATE, MONOBASIC, MONOHYDRATE 23.2 mg/4 mL; POLYSORBATE 20 1.6 mg/4 mL; WATER

HIGHLIGHTS OF PRESCRIBING INFORMATION

These highlights do not include all the information needed to use Avzivi safely and effectively. See full prescribing information for Avzivi.
Avzivi® (bevacizumab-tnjn) injection, for intravenous use
Initial U.S. Approval: 2023
Avzivi (bevacizumab-tnjn) is biosimilar to AVASTIN® (bevacizumab)

1 INDICATIONS AND USAGE

Avzivi is a vascular endothelial growth factor inhibitor indicated for the treatment of:

- Metastatic colorectal cancer, in combination with intravenous fluorouracilbased chemotherapy for first- or second-line treatment. (1.1)
- Metastatic colorectal cancer, in combination with fluoropyrimidine irinotecan- or fluoropyrimidine-oxaliplatin-based chemotherapy for second-line treatment in patients who have progressed on a first-line bevacizumab product-containing regimen. (1.1)

Limitations of Use: Avzivi is not indicated for adjuvant treatment of colon cancer. (1.1)

- Unresectable, locally advanced, recurrent or metastatic non-squamous non-small cell lung cancer, in combination with carboplatin and paclitaxel for first-line treatment. (1.2)
- Recurrent glioblastoma in adults. (1.3)
- Metastatic renal cell carcinoma in combination with interferon alfa. (1.4)
- Persistent, recurrent, or metastatic cervical cancer, in combination with paclitaxel and cisplatin, or paclitaxel and topotecan. (1.5)
- Epithelial ovarian, fallopian tube, or primary peritoneal cancer in combination with paclitaxel, pegylated liposomal doxorubicin, or topotecan for platinum-resistant recurrent disease who received no more than 2 prior chemotherapy regimens. (1.6)

2 DOSAGE AND ADMINISTRATION

Withhold for at least 28 days prior to elective surgery. Do not administer Avzivi for 28 days following major surgery and until adequate wound healing. (2.1)

- Metastatic colorectal cancer. (2.2)
- 5 mg/kg every 2 weeks with bolus-IFL
- 10 mg/kg every 2 weeks with FOLFOX4
- 5 mg/ kg every 2 weeks or 7.5 mg/kg every 3 weeks with fluoropyrimidine-irinotecan- or fluoropyrimidine-oxaliplatin-based chemotherapy after progression on a first-line bevacizumab product containing regimen

First-line non-squamous non-small cell lung cancer. (2.3)

- 15 mg/kg every 3 weeks with carboplatin and paclitaxel

Recurrent glioblastoma. (2.4)

- 10 mg/kg every 2 weeks

Metastatic renal cell carcinoma. (2.5)

- 10 mg/kg every 2 weeks with interferon alfa

Persistent, recurrent, or metastatic cervical cancer. (2.6)

- 15 mg/kg every 3 weeks with paclitaxel and cisplatin, or paclitaxel and topotecan

Platinum-resistant recurrent epithelial ovarian, fallopian tube or primary peritoneal cancer. (2.7)

- 10 mg/kg every 2 weeks with paclitaxel, pegylated liposomal doxorubicin, or topotecan given every week
- 15 mg/kg every 3 weeks with topotecan given every 3 weeks

Administer as an intravenous infusion after dilution. See full Prescribing Information for preparation and administration instructions and dosage modifications for adverse reactions. (2.8, 2.9)

3 DOSAGE FORMS AND STRENGTHS

Injection: 100 mg/4 mL (25 mg/mL) or 400 mg/16 mL (25 mg/mL) in a single-dose vial. (3)

4 CONTRAINDICATIONS

None. (4)

5 WARNINGS AND PRECAUTIONS

• Gastrointestinal Perforations and Fistula: Discontinue for gastrointestinal perforations, tracheoesophageal fistula, grade 4 fistula, or fistula formation involving any organ. (5.1)
• Surgery and Wound Healing Complications: In patients who experience wound healing complications during Avzivi treatment, withhold Avzivi until adequate wound healing. Withhold for at least 28 days prior to elective surgery. Do not administer Avzivi for at least 28 days following a major surgery, and until adequate wound healing. The safety of resumption of bevacizumab products after resolution of wound healing complication has not been established. Discontinue for wound healing complication of necrotizing fasciitis. (5.2)
• Hemorrhage: Severe or fatal hemorrhages have occurred. Do not administer for recent hemoptysis. Discontinue for Grade 3-4 hemorrhage. (5.3)
• Arterial Thromboembolic Events (ATE): Discontinue for severe ATE. (5.4)
• Venous Thromboembolic Events (VTE): Discontinue for Grade 4 VTE. (5.5)
• Hypertension: Monitor blood pressure and treat hypertension. Withhold if not medically controlled; resume once controlled. Discontinue for hypertensive crisis or hypertensive encephalopathy. (5.6)
• Posterior Reversible Encephalopathy Syndrome (PRES): Discontinue. (5.7)
• Renal Injury and Proteinuria: Monitor urine protein. Discontinue for nephrotic syndrome. Withhold until less than 2 grams of protein in urine. (5.8)
• Infusion-Related Reactions: Decrease rate for infusion-related reactions. Discontinue for severe infusion-related reactions and administer medical therapy. (5.9)
• Embryo-Fetal Toxicity: May cause fetal harm. Advise females of potential risk to fetus and need for use of effective contraception. (5.10, 8.1, 8.3)
• Ovarian Failure: Advise females of the potential risk. (5.11, 8.3)
• Congestive Heart Failure (CHF): Discontinue Avzivi in patients who develop CHF. (5.12)

6 ADVERSE REACTIONS

Most common adverse reactions incidence (incidence >10%) are epistaxis, headache, hypertension, rhinitis, proteinuria, taste alteration, dry skin, hemorrhage, lacrimation disorder, back pain and exfoliative dermatitis. (6.1)

To report SUSPECTED ADVERSE REACTIONS, contact Bio-Thera Solutions, Ltd. at 400-999-8703 or FDA at 1-800-FDA-1088 orwww.fda.gov/medwatch.

8 USE IN SPECIFIC POPULATIONS

• Lactation: Advise not to breastfeed. (8.2)

See 17 for PATIENT COUNSELING INFORMATION.

* Biosimilar means that the biological product is approved based on data demonstrating that it is highly similar to an FDA-approved biological product, known as a reference product, and that there are no clinically meaningful differences between the biosimilar product and the reference product. Biosimilarity of Avzivi has been demonstrated for the condition(s) of use (e.g. indication(s), dosing regimen(s)), strength(s), dosage form(s), and route(s) of administration described in its Full Prescribing Information.

FULL PRESCRIBING INFORMATION

1 INDICATIONS AND USAGE

1.1 Metastatic Colorectal Cancer

Avzivi, in combination with intravenous fluorouracil-based chemotherapy, is indicated for the first-or second-line treatment of patients with metastatic colorectal cancer (mCRC).

Avzivi, in combination with fluoropyrimidine-irinotecan- or fluoropyrimidine-oxaliplatin-based chemotherapy, is indicated for the second-line treatment of patients with mCRC who have progressed on a first-line bevacizumab product-containing regimen.

Limitations of Use: Avzivi is not indicated for adjuvant treatment of colon cancer [see Clinical Studies (14.2)].

1.2 First-Line Non-Squamous Non–Small Cell Lung Cancer

Avzivi, in combination with carboplatin and paclitaxel, is indicated for the first-line treatment of patients with unresectable, locally advanced, recurrent or metastatic non–squamous non–small cell lung cancer (NSCLC).

1.3 Recurrent Glioblastoma

Avzivi is indicated for the treatment of recurrent glioblastoma (GBM) in adults.

1.4 Metastatic Renal Cell Carcinoma

Avzivi, in combination with interferon alfa, is indicated for the treatment of metastatic renal cell carcinoma (mRCC).

1.5 Persistent, Recurrent, or Metastatic Cervical Cancer

Avzivi, in combination with paclitaxel and cisplatin or paclitaxel and topotecan, is indicated for the treatment of patients with persistent, recurrent, or metastatic cervical cancer.

1.6 Epithelial Ovarian, Fallopian Tube, or Primary Peritoneal Cancer

Avzivi, in combination with paclitaxel, pegylated liposomal doxorubicin, or topotecan, is indicated for the treatment of patients with platinum-resistant recurrent epithelial ovarian, fallopian tube or primary peritoneal cancer who received no more than 2 prior chemotherapy regimens.

2 DOSAGE AND ADMINISTRATION

2.1 Important Administration Information

Withhold for at least 28 days prior to elective surgery. Do not administer Avzivi until at least 28 days following major surgery and until adequate wound healing.

2.2 Metastatic Colorectal Cancer

The recommended dosage when Avzivi is administered in combination with intravenous fluorouracil-based chemotherapy is:
• 5 mg/kg intravenously every 2 weeks in combination with bolus-IFL.
• 10 mg/kg intravenously every 2 weeks in combination with FOLFOX4.
• 5 mg/kg intravenously every 2 weeks or 7.5 mg/kg intravenously every 3 weeks in combination with fluoropyrimidine-irinotecan- or fluoropyrimidine-oxaliplatin-based chemotherapy in patients who have progressed on a first-line bevacizumab product-containing regimen.

2.3 First-Line Non-Squamous Non-Small Cell Lung Cancer

The recommended dosage is 15 mg/kg intravenously every 3 weeks in combination with carboplatin and paclitaxel.

2.4 Recurrent Glioblastoma

The recommended dosage is 10 mg/kg intravenously every 2 weeks.

2.5 Metastatic Renal Cell Carcinoma

The recommended dosage is 10 mg/kg intravenously every 2 weeks in combination with interferon alfa.

2.6 Persistent, Recurrent, or Metastatic Cervical Cancer

The recommended dosage is 15 mg/kg intravenously every 3 weeks in combination with paclitaxel and cisplatin or in combination with paclitaxel and topotecan.

2.7 Epithelial Ovarian, Fallopian Tube or Primary Peritoneal Cancer

Recurrent Disease

Platinum Resistant

The recommended dosage is 10 mg/kg intravenously every 2 weeks in combination with paclitaxel, pegylated liposomal doxorubicin, or topotecan (every week).

The recommended dosage is 15 mg/kg intravenously every 3 weeks in combination with topotecan (every 3 weeks).

2.8 Dosage Modifications for Adverse Reactions

Table 1 describes dosage modifications for specific adverse reactions. No dose reductions for Avzivi are recommended.

Table 1: Dosage Modifications for Adverse Reactions

Adverse Reaction | Severity |  | Dosage Modification
Gastrointestinal Perforations and Fistulae [see Warnings and Precautions (5.1)]. | - Gastrointestinal perforation, any grade - Tracheoesophageal fistula, any grade - Fistula, Grade 4 - Fistula formation involving any internal organ |  | Discontinue Avzivi
Wound Healing; Complications [see Warnings and Precautions (5.2)]. | - Any |  | Withhold Avzivi until adequate wound healing. The safety of resumption of bevacizumab products after resolution of wound healing complications has not been established.
Wound Healing; Complications [see Warnings and Precautions (5.2)]. | - Necrotizing fasciitis |  | Discontinue Avzivi
Hemorrhage [see Warnings and Precautions (5.3)]. | - Grade 3 or 4 |  | Discontinue Avzivi
Hemorrhage [see Warnings and Precautions (5.3)]. | - Recent history of hemoptysis of 1/2 teaspoon (2.5 mL) or more |  | Withhold Avzivi
Thromboembolic Events [see Warnings and Precautions (5.4, 5.5)]. | - Arterial thromboembolism, severe |  | Discontinue Avzivi
Thromboembolic Events [see Warnings and Precautions (5.4, 5.5)]. | - Venous thromboembolism, Grade 4 |  | Discontinue Avzivi
Hypertension [see Warnings and Precautions (5.6)]. | - Hypertensive crisis - Hypertensive encephalopathy |  | Discontinue Avzivi
Hypertension [see Warnings and Precautions (5.6)]. | - Hypertension, severe |  | Withhold Avzivi if not controlled with medical management; resume once controlled
Posterior Reversible Encephalopathy Syndrome (PRES) [see Warnings and Precautions (5.7)]. | - Any |  | Discontinue Avzivi
Renal Injury and Proteinuria [see Warnings and Precautions (5.8)]. | - Nephrotic syndrome |  | Discontinue Avzivi
Renal Injury and Proteinuria [see Warnings and Precautions (5.8)]. | - Proteinuria greater than or equal to 2 grams per 24 hours in absence of nephrotic syndrome |  | Withhold Avzivi until proteinuria less than 2 grams per 24 hours
Infusion-Related Reactions [see Warnings and Precautions (5.9)]. | - Severe |  | Discontinue Avzivi
Infusion-Related Reactions [see Warnings and Precautions (5.9)]. | - Clinically significant |  | Interrupt infusion; resume at a decreased rate of infusion after symptoms resolve
Infusion-Related Reactions [see Warnings and Precautions (5.9)]. | - Mild, clinically insignificant |  | Decrease infusion rate
Congestive Heart Failure [see Warnings and Precautions (5.12)]. | Any |  | Discontinue Avzivi

2.9 Preparation and Administration

Preparation

- Use appropriate aseptic technique.
- Use sterile needle and syringe to prepare Avzivi.
- Visually inspect vial for particulate matter and discoloration prior to preparation for administration. Discard vial if solution is cloudy, discolored or contains particulate matter.
- Withdraw necessary amount of Avzivi and dilute in a total volume of 100 mL of 0.9% Sodium Chloride Injection, USP. DO NOT ADMINISTER OR MIX WITH DEXTROSE SOLUTION.
- Discard any unused portion left in a vial, as the product contains no preservatives.
- Diluted Avzivi solution may be stored at 2°C to 8°C (36°F to 46°F) for up to 8 hours, if not used immediately.
- No incompatibilities between Avzivi and polyvinylchloride or polyolefin bags have been observed.

Administration

- Administer as an intravenous infusion.
- First infusion: Administer infusion over 90 minutes.
- Subsequent infusions: Administer second infusion over 60 minutes if first infusion is tolerated. Administer all subsequent infusions over 30 minutes if second infusion over 60 minutes is tolerated.

3 DOSAGE FORMS AND STRENGTHS

Injection: 100 mg/4 mL (25 mg/mL) or 400 mg/16 mL (25 mg/mL) clear to slightly opalescent, colorless to pale brown solution in a single-dose vial.

4 CONTRAINDICATIONS

None.

5 WARNINGS AND PRECAUTIONS

5.1 Gastrointestinal Perforations and Fistulae

Serious, and sometimes fatal, gastrointestinal perforation occurred at a higher incidence in patients receiving bevacizumab products compared to patients receiving chemotherapy. The incidence ranged from 0.3% to 3% across clinical studies, with the highest incidence in patients with a history of prior pelvic radiation. Perforation can be complicated by intra-abdominal abscess, fistula formation, and the need for diverting ostomies. The majority of perforations occurred within 50 days of the first dose [see Adverse Reactions (6.1)] .

Serious fistulae (including, tracheoesophageal, bronchopleural, biliary, vaginal, renal and bladder sites) occurred at a higher incidence in patients receiving bevacizumab products compared to patients receiving chemotherapy. The incidence ranged from <1% to 1.8% across clinical studies, with the highest incidence in patients with cervical cancer. The majority of fistulae occurred within 6 months of the first dose. Patients who develop a gastrointestinal vaginal fistula may also have a bowel obstruction and require surgical intervention, as well as a diverting ostomy.

Avoid Avzivi in patients with ovarian cancer who have evidence of recto-sigmoid involvement by pelvic examination or bowel involvement on CT scan or clinical symptoms of bowel obstruction. Discontinue in patients who develop gastrointestinal perforation, tracheoesophageal fistula or any Grade 4 fistula. Discontinue in patients with fistula formation involving any internal organ .

5.2 Surgery and Wound Healing Complications

In a controlled clinical study in which bevacizumab was not administered within 28 days of major surgical procedures, the incidence of wound healing complications, including serious and fatal complications, was 15% in patients with mCRC who underwent surgery while receiving bevacizumab and 4% in patients who did not receive bevacizumab. In a controlled clinical study in patients with relapsed or recurrent GBM, the incidence of wound healing events was 5% in patients who received bevacizumab and 0.7% in patients who did not receive bevacizumab [see Adverse Reactions (6.1)].

In patients who experience wound healing complications during Avzivi treatment, withhold Avzivi until adequate wound healing. Withhold for at least 28 days prior to elective surgery. Do not administer for at least 28 days following major surgery and until adequate wound healing. The safety of resumption of bevacizumab products after resolution of wound healing complications has not been established [see Dosage and Administration (2.9)].

Necrotizing fasciitis including fatal cases, has been reported in patients receiving bevacizumab, usually secondary to wound healing complications, gastrointestinal perforation or fistula formation. Discontinue Avzivi in patients who develop necrotizing fasciitis.

5.3 Hemorrhage

Bevacizumab products can result in two distinct patterns of bleeding: minor hemorrhage, which is most commonly Grade 1 epistaxis, and serious hemorrhage, which in some cases has been fatal. Severe or fatal hemorrhage, including hemoptysis, gastrointestinal bleeding, hematemesis, CNS hemorrhage, epistaxis, and vaginal bleeding, occurred up to 5-fold more frequently in patients receiving bevacizumab compared to patients receiving chemotherapy alone. Across clinical studies, the incidence of Grades 3-5 hemorrhagic events ranged from 0.4% to 7% in patients receiving bevacizumab [see Adverse Reactions (6.1)].

Serious or fatal pulmonary hemorrhage occurred in 31% of patients with squamous NSCLC and 4% of patients with non-squamous NSCLC receiving bevacizumab with chemotherapy compared to none of the patients receiving chemotherapy alone.

Do not administer Avzivi to patients with recent history of hemoptysis of 1/2 teaspoon or more of red blood. Discontinue in patients who develop a Grades 3-4 hemorrhage.

5.4 Arterial Thromboembolic Events

Serious, sometimes fatal, arterial thromboembolic events (ATE) including cerebral infarction, transient ischemic attacks, myocardial infarction, and angina, occurred at a higher incidence in patients receiving bevacizumab compared to patients receiving chemotherapy. Across clinical studies, the incidence of Grades 3-5 ATE was 5% in patients receiving bevacizumab with chemotherapy compared to ≤2% in patients receiving chemotherapy alone; the highest incidence occurred in patients with GBM. The risk of developing ATE was increased in patients with a history of arterial thromboembolism, diabetes, or >65 years [see Use in Specific Populations (8.5)].

Discontinue in patients who develop a severe ATE. The safety of reinitiating bevacizumab products after an ATE is resolved is not known.

5.5 Venous Thromboembolic Events

An increased risk of venous thromboembolic events (VTE) was observed across clinical studies [see Adverse Reactions (6.1)] . In Study GOG-0240, Grades 3-4 VTE occurred in 11% of patients receiving bevacizumab with chemotherapy compared with 5% of patients receiving chemotherapy alone. In EORTC 26101, the incidence of Grades 3-4 VTE was 5% in patients receiving bevacizumab with chemotherapy compared to 2% in patients receiving chemotherapy alone.

Discontinue Avzivi in patients with a Grade 4 VTE, including pulmonary embolism.

5.6 Hypertension

Severe hypertension occurred at a higher incidence in patients receiving bevacizumab products as compared to patients receiving chemotherapy alone. Across clinical studies, the incidence of Grades 3-4 hypertension ranged from 5% to 18%.

Monitor blood pressure every two to three weeks during treatment with Avzivi. Treat with appropriate anti-hypertensive therapy and monitor blood pressure regularly. Continue to monitor blood pressure at regular intervals in patients with Avzivi-induced or -exacerbated hypertension after discontinuing Avzivi. Withhold Avzivi in patients with severe hypertension that is not controlled with medical management; resume once controlled with medical management. Discontinue in patients who develop hypertensive crisis or hypertensive encephalopathy.

5.7 Posterior Reversible Encephalopathy Syndrome

Posterior reversible encephalopathy syndrome (PRES) was reported in < 0.5% of patients across clinical studies. The onset of symptoms occurred from 16 hours to 1 year after the first dose. PRES is a neurological disorder which can present with headache, seizure, lethargy, confusion, blindness and other visual and neurologic disturbances. Mild to severe hypertension may be present. Magnetic resonance imaging is necessary to confirm the diagnosis of PRES.

Discontinue Avzivi in patients who develop PRES. Symptoms usually resolve or improve within days after discontinuing bevacizumab products, although some patients have experienced ongoing neurologic sequelae. The safety of reinitiating bevacizumab products in patients who developed PRES is not known.

5.8 Renal Injury and Proteinuria

The incidence and severity of proteinuria was higher in patients receiving bevacizumab as compared to patients receiving chemotherapy. Grade 3 (defined as urine dipstick 4+ or >3.5 grams of protein per 24 hours) to Grade 4 (defined as nephrotic syndrome) ranged from 0.7% to 7% in clinical studies. The overall incidence of proteinuria (all grades) was only adequately assessed in Study BO17705, in which the incidence was 20%. Median onset of proteinuria was 5.6 months (15 days to 37 months) after initiating bevacizumab. Median time to resolution was 6.1 months (95% CI: 2.8, 11.3). Proteinuria did not resolve in 40% of patients after median follow-up of 11.2 months and required discontinuation of bevacizumab in 30% of the patients who developed proteinuria [see Adverse Reactions (6.1)] .

In an exploratory, pooled analysis of patients from seven randomized clinical studies, 5% of patients receiving bevacizumab with chemotherapy experienced Grades 2-4 (defined as urine dipstick 2+ or greater or >1 gram of protein per 24 hours or nephrotic syndrome) proteinuria. Grades 2-4 proteinuria resolved in 74% of patients. Bevacizumab was reinitiated in 42% of patients. Of the 113 patients who reinitiated bevacizumab, 48% experienced a second episode of Grades 2-4 proteinuria.

Nephrotic syndrome occurred in <1% of patients receiving bevacizumab across clinical studies, in some instances with fatal outcome. In a published case series, kidney biopsy of 6 patients with proteinuria showed findings consistent with thrombotic microangiopathy. Results of a retrospective analysis of 5805 patients who received bevacizumab with chemotherapy and 3713 patients who received chemotherapy alone, showed higher rates of elevated serum creatinine levels (between 1.5 to 1.9 times baseline levels) in patients who received bevacizumab. Serum creatinine levels did not return to baseline in approximately one-third of patients who received bevacizumab.

Monitor proteinuria by dipstick urine analysis for the development or worsening of proteinuria with serial urinalyses during Avzivi therapy. Patients with a 2+ or greater urine dipstick reading should undergo further assessment with a 24-hour urine collection. Withhold for proteinuria greater than or equal to 2 grams per 24 hours and resume when less than 2 grams per 24 hours. Discontinue in patients who develop nephrotic syndrome.

Data from a postmarketing safety study showed poor correlation between UPCR (Urine Protein/Creatinine Ratio) and 24-hour urine protein [Pearson Correlation 0.39 (95% CI: 0.17, 0.57)].

5.9 Infusion-Related Reactions

Infusion-related reactions reported across clinical studies and postmarketing experience include hypertension, hypertensive crises associated with neurologic signs and symptoms, wheezing, oxygen desaturation, Grade 3 hypersensitivity, anaphylactoid/anaphylactic reactions, chest pain, headaches, rigors, and diaphoresis. In clinical studies, infusion-related reactions with the first dose occurred in <3% of patients and severe reactions occurred in 0.4% of patients.

Decrease the rate of infusion for mild, clinically insignificant infusion-related reactions. Interrupt the infusion in patients with clinically significant infusion-related reactions and consider resuming at a slower rate following resolution. Discontinue in patients who develop a severe infusion-related reaction and administer appropriate medical therapy (e.g., epinephrine, corticosteroids, intravenous antihistamines, bronchodilators and/or oxygen).

5.10 Embryo-Fetal Toxicity

Based on its mechanism of action and findings from animal studies, bevacizumab products may cause fetal harm when administered to pregnant women. Congenital malformations were observed with the administration of bevacizumab to pregnant rabbits during organogenesis every 3 days at a dose as low as a clinical dose of 10 mg/kg. Furthermore, animal models link angiogenesis and VEGF and VEGFR2 to critical aspects of female reproduction, embryo-fetal development, and postnatal development. Advise pregnant women of the potential risk to a fetus. Advise females of reproductive potential to use effective contraception during treatment with Avzivi and for 6 months after the last dose [see Use in Specific Populations (8.1, 8.3)].

5.11 Ovarian Failure

The incidence of ovarian failure was 34% vs. 2% in premenopausal women receiving bevacizumab with chemotherapy as compared to those receiving chemotherapy alone for adjuvant treatment of a solid tumor. After discontinuing bevacizumab, recovery of ovarian function at all time points during the post-treatment period was demonstrated in 22% of women receiving bevacizumab. Recovery of ovarian function is defined as resumption of menses, a positive serum β-HCG pregnancy test, or an FSH level <30 mIU/mL during the post-treatment period. Long-term effects of bevacizumab products on fertility are unknown. Inform females of reproductive potential of the risk of ovarian failure prior to initiating Avzivi [see Adverse Reactions (6.1), Use in Specific Populations (8.3)].

5.12 Congestive Heart Failure (CHF)

Avzivi is not indicated for use with anthracycline-based chemotherapy. The incidence of Grade >3 left ventricular dysfunction was 1% in patients receiving bevacizumab compared to 0.6% of patients receiving chemotherapy alone. Among patients who received prior anthracycline treatment, the rate of CHF was 4% for patients receiving bevacizumab with chemotherapy as compared to 0.6% for patients receiving chemotherapy alone.

In previously untreated patients with a hematological malignancy, the incidence of CHF and decline in left ventricular ejection fraction (LVEF) were increased in patients receiving bevacizumab with anthracycline-based chemotherapy compared to patients receiving placebo with the same chemotherapy regimen. The proportion of patients with a decline in LVEF from baseline of ≥20% or a decline from baseline of 10% to <50%, was 10% in patients receiving bevacizumab with chemotherapy compared to 5% in patients receiving chemotherapy alone.

Time to onset of left-ventricular dysfunction or CHF was 1 to 6 months after the first dose in at least 85% of the patients and was resolved in 62% of the patients who developed CHF in the bevacizumab arm compared to 82% in the placebo arm. Discontinue Avzivi in patients who develop CHF.

6 ADVERSE REACTIONS

The following clinically significant adverse reactions are described elsewhere in the labeling:

- Gastrointestinal Perforations and Fistulae [see Warnings and Precautions (5.1)] .
- Surgery and Wound Healing Complications [see Warnings and Precautions (5.2)].
- Hemorrhage [see Warnings and Precautions (5.3)].
- Arterial Thromboembolic Events [see Warnings and Precautions (5.4)].
- Venous Thromboembolic Events [see Warnings and Precautions (5.5)].
- Hypertension [see Warnings and Precautions (5.6)].
- Posterior Reversible Encephalopathy Syndrome [see Warnings and Precautions (5.7)].
- Renal Injury and Proteinuria [see Warnings and Precautions (5.8)].
- Infusion-Related Reactions [see Warnings and Precautions (5.9)].
- Ovarian Failure [see Warnings and Precautions (5.11)].
- Congestive Heart Failure [see Warnings and Precautions (5.12)].

6.1 Clinical Trials Experience

Because clinical studies are conducted under widely varying conditions, adverse reaction rates observed in the clinical studies of a drug cannot be directly compared to rates in the clinical studies of another drug and may not reflect the rates observed in practice.

The safety data in Warnings and Precautions and described below reflect exposure to bevacizumab in 4463 patients including those with mCRC (AVF2107g, E3200), non-squamous NSCLC (E4599), GBM (EORTC 26101), mRCC (BO17705), cervical cancer (GOG-0240), epithelial ovarian, fallopian tube, or primary peritoneal cancer (MO22224), or other cancers at the recommended dose and schedule for a median of 6 to 23 doses. The most common adverse reactions observed in patients receiving bevacizumab as a single agent or in combination with other anti-cancer therapies at a rate >10% were epistaxis, headache, hypertension, rhinitis, proteinuria, taste alteration, dry skin, hemorrhage, lacrimation disorder, back pain, and exfoliative dermatitis.

Across clinical studies, bevacizumab was discontinued in 8% to 22% of patients because of adverse reactions [see Clinical Studies (14)].

Metastatic Colorectal Cancer

In Combination with bolus-IFL

The safety of bevacizumab was evaluated in 392 patients who received at least one dose of bevacizumab in a double-blind, active-controlled study (AVF2107g), which compared bevacizumab (5 mg/kg every 2 weeks) with bolus-IFL to placebo with bolus-IFL in patients with mCRC [see Clinical Studies (14.1)] . Patients were randomized (1:1:1) to placebo with bolus-IFL, bevacizumab with bolus-IFL, or bevacizumab with fluorouracil and leucovorin. The demographics of the safety population were similar to the demographics of the efficacy population. All Grades 3−4 adverse reactions and selected Grades 1−2 adverse reactions (i.e., hypertension, proteinuria, thromboembolic events) were collected in the entire study population. Adverse reactions are presented in Table 2.

Table 2: Grades 3-4 Adverse Reactions Occurring at Higher Incidence (≥2%) in Patients Receiving Bevacizumab vs. Placebo in Study AVF2107g

Adverse Reactiona | Bevacizumab with IFL; (N=392) | Placebo with IFL; (N=396)
Hematology
Leukopenia | 37% | 31%
Neutropenia | 21% | 14%
Gastrointestinal
Diarrhea | 34% | 25%
Abdominal pain | 8% | 5%
Constipation | 4% | 2%
Vascular
Hypertension | 12% | 2%
Deep vein thrombosis | 9% | 5%
Intra-abdominal thrombosis | 3% | 1%
Syncope | 3% | 1%
General
Asthenia | 10% | 7%
Pain | 8% | 5%

aNCI-CTC version 3

In Combination with FOLFOX4

The safety of bevacizumab was evaluated in 521 patients in an open-label, active-controlled study (E3200) in patients who were previously treated with irinotecan and fluorouracil for initial therapy for mCRC. Patients were randomized (1:1:1) to FOLFOX4, bevacizumab (10 mg/kg every 2 weeks prior to FOLFOX4 on Day 1) with FOLFOX4, or bevacizumab alone (10 mg/kg every 2 weeks). Bevacizumab was continued until disease progression or unacceptable toxicity.

The demographics of the safety population were similar to the demographics of the efficacy population.

Selected Grades 3−5 non-hematologic and Grades 4−5 hematologic occurring at a higher incidence (≥2%) in patients receiving bevacizumab with FOLFOX4 compared to FOLFOX4 alone were fatigue (19% vs. 13%), diarrhea (18% vs. 13%), sensory neuropathy (17% vs. 9%), nausea (12% vs. 5%), vomiting (11% vs. 4%), dehydration (10% vs. 5%), hypertension (9% vs. 2%), abdominal pain (8% vs. 5%), hemorrhage (5% vs. 1%), other neurological (5% vs. 3%), ileus (4% vs. 1%) and headache (3% vs. 0%). These data are likely to under-estimate the true adverse reaction rates due to the reporting mechanisms.

First-Line Non Squamous Non-Small Cell Lung Cancer

The safety of bevacizumab was evaluated as first-line treatment in 422 patients with unresectable NSCLC who received at least one dose of bevacizumab in an active-controlled, open-label, multicenter trial (E4599) [see Clinical Studies (14.3)] . Chemotherapy naïve patients with locally advanced, metastatic or recurrent non–squamous NSCLC were randomized (1:1) to receive six 21-day cycles of paclitaxel and carboplatin with or without bevacizumab (15 mg/kg every 3 weeks). After completion or upon discontinuation of chemotherapy, patients randomized to receive bevacizumab continued to receive bevacizumab alone until disease progression or until unacceptable toxicity. The trial excluded patients with predominant squamous histology (mixed cell type tumors only), CNS metastasis, gross hemoptysis (1/2 teaspoon or more of red blood), unstable angina, or receiving therapeutic anticoagulation. The demographics of the safety population were similar to the demographics of the efficacy population.

Only Grades 3-5 non-hematologic and Grades 4-5 hematologic adverse reactions were collected. Grades 3-5 non-hematologic and Grades 4-5 hematologic adverse reactions occurring at a higher incidence (≥2%) in patients receiving bevacizumab with paclitaxel and carboplatin compared with patients receiving chemotherapy alone were neutropenia (27% vs. 17%), fatigue (16% vs. 13%), hypertension (8% vs. 0.7%), infection without neutropenia (7% vs. 3%), venous thromboembolism (5% vs. 3%), febrile neutropenia (5% vs. 2%), pneumonitis/pulmonary infiltrates (5% vs. 3%), infection with Grade 3 or 4 neutropenia (4% vs. 2%), hyponatremia (4% vs. 1%), headache (3% vs. 1%) and proteinuria (3% vs. 0%).

Recurrent Glioblastoma

The safety of bevacizumab was evaluated in a multicenter, randomized, open-label study (EORTC 26101) in patients with recurrent GBM following radiotherapy and temozolomide of whom 278 patients received at least one dose of bevacizumab and are considered safety evaluable [see Clinical Studies (14.4)] . Patients were randomized (2:1) to receive bevacizumab (10 mg/kg every 2 weeks) with lomustine or lomustine alone until disease progression or unacceptable toxicity. The demographics of the safety population were similar to the demographics of the efficacy population. In the bevacizumab with lomustine arm, 22% of patients discontinued treatment due to adverse reactions compared with 10% of patients in the lomustine arm. In patients receiving bevacizumab with lomustine, the adverse reaction profile was similar to that observed in other approved indications.

Metastatic Renal Cell Carcinoma

The safety of bevacizumab was evaluated in 337 patients who received at least one dose of bevacizumab in a multicenter, double-blind study (BO17705) in patients with mRCC. Patients who had undergone a nephrectomy were randomized (1:1) to receive either bevacizumab (10 mg/kg every 2 weeks) or placebo with interferon alfa [see Clinical Studies (14.5)] . Patients were treated until disease progression or unacceptable toxicity. The demographics of the safety population were similar to the demographics of the efficacy population.

Grades 3-5 adverse reactions occurring at a higher incidence (≥2%) were fatigue (13% vs. 8%), asthenia (10% vs. 7%), proteinuria (7% vs. 0%), hypertension (6% vs. 1%; including hypertension and hypertensive crisis), and hemorrhage (3% vs. 0.3%; including epistaxis, small intestinal hemorrhage, aneurysm ruptured, gastric ulcer hemorrhage, gingival bleeding, hemoptysis, hemorrhage intracranial, large intestinal hemorrhage, respiratory tract hemorrhage, and traumatic hematoma). Adverse reactions are presented in Table 3.

Table 3: Grades 1-5 Adverse Reactions Occurring at Higher Incidence (≥5%) of Patients Receiving Bevacizumab vs. Placebo with Interferon Alfa in Study BO17705

Adverse Reactiona | Bevacizumab with Interferon; Alfa; (N=337) | Placebo with Interferon; Alfa; (N=304)
Metabolism and nutrition
Decreased appetite | 36% | 31%
Weight loss | 20% | 15%
General
Fatigue | 33% | 27%
Vascular
Hypertension | 28% | 9%
Respiratory, thoracic and mediastinal
Epistaxis | 27% | 4%
Dysphonia | 5% | 0%
Nervous system
Headache | 24% | 16%
Gastrointestinal
Diarrhea | 21% | 16%
Renal and urinary
Proteinuria | 20% | 3%
Musculoskeletal and connective tissue
Myalgia | 19% | 14%
Back pain | 12% | 6%

aNCI-CTC version 3

The following adverse reactions were reported at a 5-fold greater incidence in patients receiving bevacizumab with interferon-alfa compared to patients receiving placebo with interferon-alfa and not represented in Table 3: gingival bleeding (13 patients vs. 1 patient); rhinitis (9 vs. 0); blurred vision (8 vs. 0); gingivitis (8 vs. 1); gastroesophageal reflux disease (8 vs. 1); tinnitus (7 vs. 1); tooth abscess (7 vs. 0); mouth ulceration (6 vs. 0); acne (5 vs. 0); deafness (5 vs. 0); gastritis (5 vs. 0); gingival pain (5 vs. 0) and pulmonary embolism (5 vs. 1).

Persistent, Recurrent, or Metastatic Cervical Cancer

The safety of bevacizumab was evaluated in 218 patients who received at least one dose of bevacizumab in a multicenter study (GOG-0240) in patients with persistent, recurrent, or metastatic cervical cancer [see Clinical Studies (14.6)] . Patients were randomized (1:1:1:1) to receive paclitaxel and cisplatin with or without bevacizumab (15 mg/kg every 3 weeks), or paclitaxel and topotecan with or without bevacizumab (15 mg/kg every 3 weeks). The demographics of the safety population were similar to the demographics of the efficacy population.

Grades 3-4 adverse reactions occurring at a higher incidence (≥2%) in 218 patients receiving bevacizumab with chemotherapy compared to 222 patients receiving chemotherapy alone were abdominal pain (12% vs. 10%), hypertension (11% vs. 0.5%), thrombosis (8% vs. 3%), diarrhea (6% vs. 3%), anal fistula (4% vs. 0%), proctalgia (3% vs. 0%), urinary tract infection (8% vs. 6%), cellulitis (3% vs. 0.5%), fatigue (14% vs. 10%), hypokalemia (7% vs. 4%), hyponatremia (4% vs. 1%), dehydration (4% vs. 0.5%), neutropenia (8% vs. 4%), lymphopenia (6% vs. 3%), back pain (6% vs. 3%), and pelvic pain (6% vs. 1%). Adverse reactions are presented in Table 4.

Table 4: Grades 1-4 Adverse Reactions Occurring at Higher Incidence (≥5%) in Patients Receiving Bevacizumab with Chemotherapy vs. Chemotherapy Alone in Study GOG-0240

Adverse Reactiona | Bevacizumab with Chemotherapy; (N=218) | Chemotherapy; (N=222)
General
Fatigue | 80% | 75%
Peripheral edema | 15% | 22%
Metabolism and nutrition
Decreased appetite | 34% | 26%
Hyperglycemia | 26% | 19%
Hypomagnesemia | 24% | 15%
Weight loss | 21% | 7%
Hyponatremia | 19% | 10%
Hypoalbuminemia | 16% | 11%
Vascular
Hypertension | 29% | 6%
Thrombosis | 10% | 3%
Infections
Urinary tract infection | 22% | 14%
Infection | 10% | 5%
Nervous system
Headache | 22% | 13%
Dysarthria | 8% | 1%
Psychiatric
Anxiety | 17% | 10%
Respiratory, thoracic and mediastinal
Epistaxis | 17% | 1%
Renal and urinary
Increased blood creatinine | 16% | 10%
Proteinuria | 10% | 3%
Gastrointestinal
Stomatitis | 15% | 10%
Proctalgia | 6% | 1%
Anal fistula | 6% | 0%
Reproductive system and breast
Pelvic pain | 14% | 8%
Hematology
Neutropenia | 12% | 6%
Lymphopenia | 12% | 5%

aNCI-CTC version 3

Epithelial Ovarian, Fallopian Tube or Primary Peritoneal Cancer

Platinum- Resistant Recurrent Epithelial Ovarian, Fallopian Tube, or Primary Peritoneal Cancer

The safety of bevacizumab was evaluated in 179 patients who received at least one dose of bevacizumab in a multicenter, open-label study (MO22224) in which patients were randomized (1:1) to bevacizumab with chemotherapy or chemotherapy alone in patients with platinum resistant, recurrent epithelial ovarian, fallopian tube, or primary peritoneal cancer that recurred within <6 months from the most recent platinum based therapy [see Clinical Studies (14.8)] . Patients were randomized to receive bevacizumab 10 mg/kg every 2 weeks or 15 mg/kg every 3 weeks. Patients had received no more than 2 prior chemotherapy regimens. The trial excluded patients with evidence of recto-sigmoid involvement by pelvic examination or bowel involvement on CT scan or clinical symptoms of bowel obstruction. Patients were treated until disease progression or unacceptable toxicity. Forty percent of patients on the chemotherapy alone arm received bevacizumab alone upon progression. The demographics of the safety population were similar to the demographics of the efficacy population.

Grades 3-4 adverse reactions occurring at a higher incidence (≥2%) in 179 patients receiving bevacizumab with chemotherapy compared to 181 patients receiving chemotherapy alone were hypertension (6.7% vs. 1.1%) and palmar-plantar erythrodysaesthesia syndrome (4.5% vs. 1.7%).

Adverse reactions are presented in Table 5.

Table 5: Grades 2−4 Adverse Reactions Occurring at Higher Incidence (≥5%) in Patients Receiving Bevacizumab with Chemotherapy vs. Chemotherapy Alone in Study MO22224

Adverse Reactiona | Bevacizumab with Chemotherapy (N=179) | Chemotherapy; (N=181)
Hematology
Neutropenia | 31% | 25%
Vascular
Hypertension | 19% | 6%
Nervous system
Peripheral sensory neuropathy | 18% | 7%
General
Mucosal inflammation | 13% | 6%
Renal and urinary
Proteinuria | 12% | 0.6%
Skin and subcutaneous tissue
Palmar-plantar erythrodysaesthesia | 11% | 5%
Infections
Infection | 11% | 4%
Respiratory, thoracic and mediastinal
Epistaxis | 5% | 0%

aNCI-CTC version 3

6.2 Immunogenicity

The observed incidence of anti-drug antibodies is highly dependent on the sensitivity and specificity of the assay. Differences in assay methods preclude meaningful comparisons of the incidence of anti-drug antibodies in the studies described below with the incidence of anti-drug antibodies in other studies, including those of bevacizumab or of other bevacizumab products.

In clinical studies for adjuvant treatment of a solid tumor, 0.6% (14/2233) of patients tested positive for treatment-emergent anti-bevacizumab antibodies as detected by an electrochemiluminescent (ECL) based assay. Among these 14 patients, three tested positive for neutralizing antibodies against bevacizumab using an enzyme-linked immunosorbent assay (ELISA). The clinical significance of these anti-bevacizumab antibodies is not known.

6.3 Postmarketing Experience

The following adverse reactions have been identified during postapproval use of bevacizumab products. Because these reactions are reported voluntarily from a population of uncertain size, it is not always possible to reliably estimate their frequency or establish a causal relationship to drug exposure.

General:Polyserositis

Cardiovascular:Pulmonary hypertension, Mesenteric venous occlusion

Gastrointestinal:Gastrointestinal ulcer, Intestinal necrosis, Anastomotic ulceration

Hemic and lymphatic:Pancytopenia

Hepatobiliary disorders:Gallbladder perforation

Musculoskeletal and Connective Tissue Disorders:Osteonecrosis of the jaw

Renal:Renal thrombotic microangiopathy (manifested as severe proteinuria)

Respiratory:Nasal septum perforation

Vascular: Arterial (including aortic) aneurysms, dissections, and rupture

7 DRUG INTERACTIONS

Effects of Avzivi on Other Drugs

No clinically meaningful effect on the pharmacokinetics of irinotecan or its active metabolite SN38, interferon alfa, carboplatin or paclitaxel was observed when bevacizumab was administered in combination with these drugs; however, 3 of the 8 patients receiving bevacizumab with paclitaxel and carboplatin had lower paclitaxel exposure after four cycles of treatment (at Day 63) than those at Day 0, while patients receiving paclitaxel and carboplatin alone had a greater paclitaxel exposure at Day 63 than at Day 0.

8 USE IN SPECIFIC POPULATIONS

8.1 Pregnancy

Risk Summary

Based on findings from animal studies and their mechanism of action [see Clinical Pharmacology (12.1)], bevacizumab products may cause fetal harm in pregnant women. Limited postmarketing reports describe cases of fetal malformations with use of bevacizumab products in pregnancy; however, these reports are insufficient to determine drug- associated risks. In animal reproduction studies, intravenous administration of bevacizumab to pregnant rabbits every 3 days during organogenesis at doses approximately 1 to 10 times the clinical dose of 10 mg/kg produced fetal resorptions, decreased maternal and fetal weight gain and multiple congenital malformations including corneal opacities and abnormal ossification of the skull and skeleton including limb and phalangeal defects (see Data). Furthermore, animal models link angiogenesis and VEGF and VEGFR2 to critical aspects of female reproduction, embryofetal development, and postnatal development. Advise pregnant women of the potential risk to a fetus.

In the U.S. general population, the estimated background risk of major birth defects and miscarriage in clinically recognized pregnancies is 2% to 4% and 15% to 20%, respectively.

Data

Animal Data

Pregnant rabbits dosed with 10 mg/kg to 100 mg/kg bevacizumab (approximately 1 to 10 times the clinical dose of 10 mg/kg) every three days during the period of organogenesis (gestation day 6−18) exhibited decreases in maternal and fetal body weights and increased number of fetal resorptions. There were dose-related increases in the number of litters containing fetuses with any type of malformation (42% for the 0 mg/kg dose, 76% for the 30 mg/kg dose, and 95% for the 100 mg/kg dose) or fetal alterations (9% for the 0 mg/kg dose, 15% for the 30 mg/kg dose, and 61% for the 100 mg/kg dose). Skeletal deformities were observed at all dose levels, with some abnormalities including meningocele observed only at the 100 mg/kg dose level. Teratogenic effects included: reduced or irregular ossification in the skull, jaw, spine, ribs, tibia and bones of the paws; fontanel, rib and hindlimb deformities; corneal opacity; and absent hindlimb phalanges.

8.2 Lactation

Risk Summary

No data are available regarding the presence of bevacizumab products in human milk, the effects on the breast fed infant, or the effects on milk production. Human IgG is present in human milk, but published data suggest that breast milk antibodies do not enter the neonatal and infant circulation in substantial amounts. Because of the potential for serious adverse reactions in breastfed infants, advise women not to breastfeed during treatment with Avzivi and for 6 months after the last dose.

8.3 Females and Males of Reproductive Potential

Contraception

Females

Bevacizumab products may cause fetal harm when administered to a pregnant woman [see Use in Specific Populations (8.1)] . Advise females of reproductive potential to use effective contraception during treatment with Avzivi and for 6 months after the last dose.

Infertility

Females

Bevacizumab products increases the risk of ovarian failure and may impair fertility. Inform females of reproductive potential of the risk of ovarian failure prior to the first-dose of Avzivi. Long-term effects of bevacizumab products on fertility are not known.

In a clinical study of 179 premenopausal women randomized to receive chemotherapy with or without bevacizumab, the incidence of ovarian failure was higher in patients who received bevacizumab with chemotherapy (34%) compared to patients who received chemotherapy alone (2%). After discontinuing bevacizumab with chemotherapy, recovery of ovarian function occurred in 22% of these patients [see Warnings and Precautions (5.11), Adverse Reactions (6.1) ].

8.4 Pediatric Use

The safety and effectiveness of Avzivi in pediatric patients have not been established.

In published literature reports, cases of non-mandibular osteonecrosis have been observed in patients under the age of 18 years who received bevacizumab. Bevacizumab products are not approved for use in patients under the age of 18 years.

Antitumor activity was not observed among eight pediatric patients with relapsed GBM who received bevacizumab and irinotecan. Addition of bevacizumab to standard of care did not result in improved event-free survival in pediatric patients enrolled in two randomized clinical studies, one in high grade glioma (n=121) and one in metastatic rhabdomyosarcoma or non-rhabdomyosarcoma soft tissue sarcoma (n=154).

Based on the population pharmacokinetics analysis of data from 152 pediatric and young adult patients with cancer (7 months to 21 years of age), bevacizumab clearance normalized by body weight in pediatrics was comparable to that in adults.

Juvenile Animal Toxicity Data

Juvenile cynomolgus monkeys with open growth plates exhibited physeal dysplasia following 4 to 26 weeks exposure at 0.4 to 20 times the recommended human dose (based on mg/kg and exposure). The incidence and severity of physeal dysplasia were dose-related and were partially reversible upon cessation of treatment.

8.5 Geriatric Use

In an exploratory pooled analysis of 1745 patients from five randomized, controlled studies, 35% of patients were ≥65 years old. The overall incidence of ATE was increased in all patients receiving bevacizumab with chemotherapy as compared to those receiving chemotherapy alone, regardless of age; however, the increase in the incidence of ATE was greater in patients ≥65 years (8% vs. 3%) as compared to patients < 65 years (2% vs. 1%) [see Warnings and Precautions (5.4)].

11 DESCRIPTION

Bevacizumab-tnjn is a vascular endothelial growth factor inhibitor. Bevacizumab-tnjn is a recombinant humanized monoclonal IgG1 antibody that contains human framework regions and murine complementarity-determining regions. Bevacizumab-tnjn has an approximate molecular weight of 149 kDa. Bevacizumab-tnjn is produced in a mammalian cell (Chinese Hamster Ovary) expression system.

Avzivi (bevacizumab-tnjn) injection is a sterile, preservative-free, clear to slightly opalescent, colorless to pale brown solution in a single-dose vial for intravenous use. Avzivi contains bevacizumab-tnjn at a concentration of 25 mg/mL in either a 100 mg/4 mL or 400 mg/16 mL single-dose vial.

Each mL of solution contains 25 mg bevacizumab-tnjn, dibasic sodium phosphate (1.2 mg), monobasic sodium phosphate (5 mg), polysorbate 20 (0.4 mg), trehalose (54.3 mg) , and Water for Injection, USP. The pH is 6.1.

12 CLINICAL PHARMACOLOGY

12.1 Mechanism of Action

Bevacizumab products bind VEGF and prevent the interaction of VEGF to its receptors (Flt-1 and KDR) on the surface of endothelial cells. The interaction of VEGF with its receptors leads to endothelial cell proliferation and new blood vessel formation in in vitro models of angiogenesis. Administration of bevacizumab to xenotransplant models of colon cancer in nude (athymic) mice caused reduction of microvascular growth and inhibition of metastatic disease progression.

12.2 Pharmacokinetics

The pharmacokinetic profile of bevacizumab was assessed using an assay that measures total serum bevacizumab concentrations (i.e., the assay did not distinguish between free bevacizumab and bevacizumab bound to VEGF ligand). Based on a population pharmacokinetic analysis of 491 patients who received 1 to 20 mg/kg of bevacizumab every week, every 2 weeks, or every 3 weeks, bevacizumab pharmacokinetics are linear and the predicted time to reach more than 90% of steady state concentration is 84 days. The accumulation ratio following a dose of 10 mg/kg of bevacizumab once every 2 weeks is 2.8.

Population simulations of bevacizumab exposures provide a median trough concentration of 80.3 mcg/mL on Day 84 (10th, 90th percentile: 45, 128) following a dose of 5 mg/kg once every two weeks.

Distribution

The mean (% coefficient of variation [CV%]) central volume of distribution is 2.9 (22%) L.

Elimination

The mean (CV%) clearance is 0.23 (33) L/day. The estimated half-life is 20 days (11 to 50 days).

Specific Populations

The clearance of bevacizumab varied by body weight, sex, and tumor burden. After correcting for body weight, males had a higher bevacizumab clearance (0.26 L/day vs. 0.21 L/day) and a larger central volume of distribution (3.2 L vs. 2.7 L) than females. Patients with higher tumor burden (at or above median value of tumor surface area) had a higher bevacizumab clearance (0.25 L/day vs. 0.20 L/day) than patients with tumor burdens below the median. In Study AVF2107g, there was no evidence of lesser efficacy (hazard ratio for overall survival) in males or patients with higher tumor burden treated with bevacizumab as compared to females and patients with low tumor burden.

13 NONCLINICAL TOXICOLOGY

13.1 Carcinogenesis, Mutagenesis, Impairment of Fertility

No studies have been conducted to assess potential of bevacizumab products for carcinogenicity or mutagenicity.

Bevacizumab products may impair fertility. Female cynomolgus monkeys treated with 0.4 to 20 times the recommended human dose of bevacizumab exhibited arrested follicular development or absent corpora lutea, as well as dose-related decreases in ovarian and uterine weights, endometrial proliferation, and the number of menstrual cycles. Following a 4- or 12-week recovery period, there was a trend suggestive of reversibility. After the 12-week recovery period, follicular maturation arrest was no longer observed, but ovarian weights were still moderately decreased. Reduced endometrial proliferation was no longer observed at the 12-week recovery time point; however, decreased uterine weight, absent corpora lutea, and reduced number of menstrual cycles remained evident.

13.2 Animal Toxicology and/or Pharmacology

Rabbits dosed with bevacizumab exhibited reduced wound healing capacity. Using full-thickness skin incision and partial thickness circular dermal wound models, bevacizumab dosing resulted in reductions in wound tensile strength, decreased granulation and re-epithelialization, and delayed time to wound closure.

14 CLINICAL STUDIES

14.1 Metastatic Colorectal Cancer

Study AVF2107g

The safety and efficacy of bevacizumab was evaluated in a double-blind, active-controlled study [AVF2107g (NCT00109070)] in 923 patients with previously untreated mCRC who were randomized (1:1:1) to placebo with bolus-IFL (irinotecan 125 mg/m^2, fluorouracil 500 mg/m^2, and leucovorin 20 mg/m^2given once weekly for 4 weeks every 6 weeks), bevacizumab (5 mg/kg every 2 weeks) with bolus-IFL, or bevacizumab (5 mg/kg every 2 weeks) with fluorouracil and leucovorin. Enrollment to the bevacizumab with fluorouracil and leucovorin arm was discontinued after enrollment of 110 patients in accordance with the protocol-specified adaptive design. Bevacizumab was continued until disease progression or unacceptable toxicity or for a maximum of 96 weeks. The main outcome measure was overall survival (OS).

The median age was 60 years; 60% were male, 79% were White, 57% had an ECOG performance status of 0, 21% had a rectal primary and 28% received prior adjuvant chemotherapy. The dominant site of disease was extra-abdominal in 56% of patients and was the liver in 38% of patients.

The addition of bevacizumab improved survival across subgroups defined by age (<65 years, ≥65 years) and sex. Results are presented in Table 6 and Figure 1.

Table 6: Efficacy Results in Study AVF2107g

Efficacy Parameter | Bevacizumab with bolus-IFL (N=402) | Placebo with bolus-IFL (N=411)
Overall Survival
Median, in months | 20.3 | 15.6
Hazard ratio; (95% CI) | 0.66; (0.54, 0.81)
p-valuea | <0.001
Progression-Free Survival
Median, in months | 10.6 | 6.2
Hazard ratio; (95% CI) | 0.54; (0.45, 0.66)
p-valuea | <0.001
Overall Response Rate
Rate (%) | 45% | 35%
p-valueb | <0.01
Duration of Response
Median, in months | 10.4 | 7.1

aby stratified log-rank test.

bby χ^2test

Figure 1: Kaplan-Meier Curves for Duration of Survival in Metastatic Colorectal Cancer in Study AVF 2107g

Among the 110 patients randomized to bevacizumab with fluorouracil and leucovorin, median OS was 18.3 months, median progression-free survival (PFS) was 8.8 months, overall response rate (ORR) was 39%, and median duration of response was 8.5 months.

Study E3200

The safety and efficacy of bevacizumab were evaluated in a randomized, open-label, active-controlled study [E3200 (NCT00025337)] in 829 patients who were previously treated with irinotecan and fluorouracil for initial therapy for metastatic disease or as adjuvant therapy. Patients were randomized (1:1:1) to FOLFOX4 (Day 1: oxaliplatin 85 mg/m^2and leucovorin 200 mg/m^2concurrently, then fluorouracil 400 mg/m^2bolus followed by 600 mg/m^2continuously; Day 2: leucovorin 200 mg/m^2, then fluorouracil 400 mg/m^2bolus followed by 600 mg/m^2continuously; every 2 weeks), bevacizumab (10 mg/kg every 2 weeks prior to FOLFOX4 on Day 1) with FOLFOX4, or bevacizumab alone (10 mg/kg every 2 weeks). Bevacizumab was continued until disease progression or unacceptable toxicity. The main outcome measure was OS.

The bevacizumab alone arm was closed to accrual after enrollment of 244 of the planned 290 patients following a planned interim analysis by the data monitoring committee based on evidence of decreased survival compared to FOLFOX4 alone.

The median age was 61 years; 60% were male, 87% were White, 49% had an ECOG performance status of 0, 26% received prior radiation therapy, and 80% received prior adjuvant chemotherapy, 99% received prior irinotecan with or without fluorouracil for metastatic disease, and 1% received prior irinotecan and fluorouracil as adjuvant therapy.

The addition of bevacizumab to FOLFOX4 resulted in significantly longer survival as compared to FOLFOX4 alone; median OS was 13.0 months vs. 10.8 months [hazard ratio (HR) 0.75 (95% CI: 0.63, 0.89), p-value of 0.001 stratified log-rank test] with clinical benefit seen in subgroups defined by age (<65 years, ≥65 years) and sex. PFS and ORR based on investigator assessment were higher in patients receiving bevacizumab with FOLFOX4.

Study TRC-0301

The activity of bevacizumab with fluorouracil (as bolus or infusion) and leucovorin was evaluated in a single arm study [TRC-0301 (NCT00066846)] enrolling 339 patients with mCRC with disease progression following both irinotecan- and oxaliplatin-based chemotherapy. Seventy-three percent of patients received concurrent bolus fluorouracil and leucovorin. One objective partial response was verified in the first 100 evaluable patients for an ORR of 1% (95% CI: 0%, 5.5%).

Study ML18147

The safety and efficacy of bevacizumab were evaluated in a prospective, randomized, open-label, multinational, controlled study [ML18147 (NCT00700102)] in 820 patients with histologically confirmed mCRC who had progressed on a first-line bevacizumab-containing regimen. Patients were excluded if they progressed within 3 months of initiating first-line chemotherapy and if they received bevacizumab for less than 3 consecutive months in the first-line setting. Patients were randomized (1:1) within 3 months after discontinuing bevacizumab as first-line treatment to receive fluoropyrimidine-irinotecan- or fluoropyrimidine-oxaliplatin-based chemotherapy with or without bevacizumab (5 mg/kg every 2 weeks or 7.5 mg/kg every 3 weeks). The choice of second-line treatment was contingent upon first-line chemotherapy. Second-line treatment was administered until progressive disease or unacceptable toxicity. The main outcome measure was OS. A secondary outcome measure was ORR.

The median age was 63 years (21 to 84 years); 64% were male, 52% had an ECOG performance status of 1, 44% had an ECOG performance status of 0, 58% received irinotecan-based therapy as first-line treatment, 55% progressed on first-line treatment within 9 months, and 77% received their last dose of bevacizumab as first-line treatment within 42 days of being randomized. Second-line chemotherapy regimens were generally balanced between each arm.

The addition of bevacizumab to fluoropyrimidine-based chemotherapy resulted in a statistically significant prolongation of OS and PFS. There was no significant difference in ORR. Results are presented in Table 7 and Figure 2.

Table 7: Efficacy Results in Study ML18147

Efficacy Parameter | Bevacizumab with Chemotherapy; (N=409) | Chemotherapy; (N=411)
Overall Survivala
Median, in months | 11.2 | 9.8
Hazard ratio (95% CI) | 0.81 (0.69, 0.94)
Progression-Free Survivalb
Median, in months | 5.7 | 4.0
Hazard ratio (95% CI) | 0.68 (0.59, 0.78)

ap=0.0057 by unstratified log-rank test.

bp-value <0.0001 by unstratified log-rank test.

Figure 2: Kaplan-Meier Curves for Duration of Survival in Metastatic Colorectal Cancer in Study ML18147

14.2 Lack of Efficacy in Adjuvant Treatment of Colon Cancer

Lack of efficacy of bevacizumab as an adjunct to standard chemotherapy for the adjuvant treatment of colon cancer was determined in two randomized, open-label, multicenter clinical studies. The first study [BO17920 (NCT00112918)] was conducted in 3451 patients with high-risk stage II and III colon cancer, who had undergone surgery for colon cancer with curative intent. Patients were randomized to receive bevacizumab at a dose equivalent to 2.5 mg/kg/week on either a 2-weekly schedule with FOLFOX4 (N=1155) or on a 3-weekly schedule with XELOX (N=1145) or FOLFOX4 alone (N=1151). The main outcome measure was disease free survival (DFS) in patients with stage III colon cancer.

The median age was 58 years; 54% were male, 84% were White and 29% were ≥65 years. Eighty-three percent had stage III disease.

The addition of bevacizumab to chemotherapy did not improve DFS. As compared to FOLFOX4 alone, the proportion of stage III patients with disease recurrence or with death due to disease progression were numerically higher for patients receiving bevacizumab with FOLFOX4 or with XELOX. The hazard ratios for DFS were 1.17 (95% CI: 0.98, 1.39) for bevacizumab with FOLFOX4 versus FOLFOX4 alone and 1.07 (95% CI: 0.90, 1.28) for bevacizumab with XELOX versus FOLFOX4 alone. The hazard ratios for OS were 1.31 (95% CI: 1.03, 1.67) and 1.27 (95% CI: 1, 1.62) for the comparison of bevacizumab with FOLFOX4 versus FOLFOX4 alone and bevacizumab with XELOX versus FOLFOX4 alone, respectively. Similar lack of efficacy for DFS was observed in the bevacizumab-containing arms compared to FOLFOX4 alone in the high-risk stage II cohort.

In a second study [NSABP-C-08 (NCT00096278)], patients with stage II and III colon cancer who had undergone surgery with curative intent, were randomized to receive either bevacizumab administered at a dose equivalent to 2.5 mg/kg/week with mFOLFOX6 (N=1354) or mFOLFOX6 alone (N=1356). The median age was 57 years, 50% were male and 87% White. Seventy-five percent had stage III disease. The main outcome was DFS among stage III patients. The HR for DFS was 0.92 (95% CI: 0.77, 1.10). OS was not significantly improved with the addition of bevacizumab to mFOLFOX6 [HR 0.96 (95% CI: 0.75, 1.22)].

14.3 First-Line Non–Squamous Non–Small Cell Lung Cancer

Study E4599

The safety and efficacy of bevacizumab as first-line treatment of patients with locally advanced, metastatic, or recurrent non–squamous NSCLC was studied in a single, large, randomized, active-controlled, open-label, multicenter study [E4599 (NCT00021060)]. A total of 878 chemotherapy-naïve patients with locally advanced, metastatic or recurrent non–squamous NSCLC were randomized (1:1) to receive six 21-day cycles of paclitaxel (200 mg/m^2) and carboplatin (AUC 6) with or without bevacizumab 15 mg/kg. After completing or discontinuing chemotherapy, patients randomized to receive bevacizumab continued to receive bevacizumab alone until disease progression or until unacceptable toxicity. The trial excluded patients with predominant squamous histology (mixed cell type tumors only), CNS metastasis, gross hemoptysis (1/2 teaspoon or more of red blood), unstable angina, or receiving therapeutic anticoagulation. The main outcome measure was duration of survival.

The median age was 63 years; 54% were male, 43% were ≥65 years, and 28% had ≥5% weight loss at study entry. Eleven percent had recurrent disease. Of the 89% with newly diagnosed NSCLC, 12% had Stage IIIB with malignant pleural effusion and 76% had Stage IV disease.

OS was statistically significantly longer for patients receiving bevacizumab with paclitaxel and carboplatin compared with those receiving chemotherapy alone. Median OS was 12.3 months vs. 10.3 months [HR 0.80 (95% CI: 0.68, 0.94), final p-value of 0.013, stratified log-rank test]. Based on investigator assessment which was not independently verified, patients were reported to have longer PFS with bevacizumab with paclitaxel and carboplatin compared to chemotherapy alone. Results are presented in Figure 3.

Figure 3: Kaplan-Meier Curves for Duration of Survival in First-Line Non-Squamous Non-Small Cell Lung Cancer in Study E4599

In an exploratory analysis across patient subgroups, the impact of bevacizumab on OS was less robust in the following subgroups: women [HR 0.99 (95% CI: 0.79, 1.25)], patients ≥65 years [HR 0.91 (95% CI: 0.72, 1.14)] and patients with ≥5% weight loss at study entry [HR 0.96 (95% CI: 0.73, 1.26)].

Study BO17704

The safety and efficacy of bevacizumab in patients with locally advanced, metastatic or recurrent non-squamous NSCLC, who had not received prior chemotherapy was studied in another randomized, double-blind, placebo-controlled study [BO17704 (NCT00806923)]. A total of 1043 patients were randomized (1:1:1) to receive cisplatin and gemcitabine with placebo, bevacizumab 7.5 mg/kg or bevacizumab 15 mg/kg. The main outcome measure was PFS. Secondary outcome measure was OS.

The median age was 58 years; 36% were female and 29% were ≥65 years. Eight percent had recurrent disease and 77% had Stage IV disease.

PFS was significantly higher in both bevacizumab-containing arms compared to the placebo arm [HR 0.75 (95% CI: 0.62, 0.91), p-value of 0.0026 for bevacizumab 7.5 mg/kg and HR 0.82 (95% CI: 0.68; 0.98), p-value of 0.0301 for bevacizumab 15 mg/kg]. The addition of bevacizumab to cisplatin and gemcitabine failed to demonstrate an improvement in the duration of OS [HR 0.93 (95% CI: 0.78; 1.11), p-value of 0.420 for bevacizumab 7.5 mg/kg and HR 1.03 (95% CI: 0.86, 1.23), p-value of 0.761 for bevacizumab 15 mg/kg] .

14.4 Recurrent Glioblastoma

Study EORTC 26101

The safety and efficacy of bevacizumab were evaluated in a multicenter, randomized (2:1), open-label study in patients with recurrent GBM (EORTC 26101, NCT01290939). Patients with first progression following radiotherapy and temozolomide were randomized (2:1) to receive bevacizumab (10 mg/kg every 2 weeks) with lomustine (90 mg/m^2every 6 weeks) or lomustine (110 mg/m^2every 6 weeks) alone until disease progression or unacceptable toxicity. Randomization was stratified by World Health Organization performance status (0 vs. >0), steroid use (yes vs. no), largest tumor diameter (≤40 vs. >40 mm), and institution. The main outcome measure was OS. Secondary outcome measures were investigator-assessed PFS and ORR per the modified Response Assessment in Neuro-oncology (RANO) criteria, health related quality of life (HRQoL), cognitive function, and corticosteroid use.

A total of 432 patients were randomized to receive lomustine alone (N=149) or bevacizumab with lomustine (N=283). The median age was 57 years; 24.8% of patients were ≥65 years. The majority of patients with were male (61%); 66% had a WHO performance status score >0; and in 56% the largest tumor diameter was ≤40 mm. Approximately 33% of patients randomized to receive lomustine received bevacizumab following documented progression.

No difference in OS (HR 0.91, p -value of 0.4578) was observed between arms; therefore, all secondary outcome measures are descriptive only. PFS was longer in the bevacizumab with lomustine arm [HR 0.52 (95% CI: 0.41, 0.64)] with a median PFS of 4.2 months in the bevacizumab with lomustine arm and 1.5 months in the lomustine arm. Among the 50% of patients receiving corticosteroids at the time of randomization, a higher percentage of patients in the bevacizumab with lomustine arm discontinued corticosteroids (23% vs. 12%).

Study AVF3708g and Study NCI 06-C-0064E

The efficacy and safety of bevacizumab 10 mg/kg every 2 weeks in patients with previously treated GBM were evaluated in one single arm single center study (NCI 06-C-0064E) and a randomized noncomparative multicenter study [AVF3708g (NCT00345163)]. Response rates in both studies were evaluated based on modified WHO criteria that considered corticosteroid use. In AVF3708g, the response rate was 25.9% (95% CI: 17%, 36.1%) with a median duration of response of 4.2 months (95% CI: 3, 5.7). In Study NCI 06-C-0064E, the response rate was 19.6% (95% CI: 10.9%, 31.3%) with a median duration of response of 3.9 months (95% CI: 2.4, 17.4).

14.5 Metastatic Renal Cell Carcinoma

Study BO17705

The safety and efficacy of bevacizumab were evaluated in patients with treatment-naïve mRCC in a multicenter, randomized, double-blind, international study [BO17705 (NCT00738530)] comparing interferon alfa and bevacizumab versus interferon alfa and placebo. A total of 649 patients who had undergone a nephrectomy were randomized (1:1) to receive either bevacizumab (10 mg/kg every 2 weeks; N=327) or placebo (every 2 weeks; N=322) with interferon alfa (9 MIU subcutaneously three times weekly for a maximum of 52 weeks). Patients were treated until disease progression or unacceptable toxicity. The main outcome measure was investigator-assessed PFS. Secondary outcome measures were ORR and OS.

The median age was 60 years (18 to 82 years); 70% were male and 96% were White. The study population was characterized by Motzer scores as follows: 28% favorable (0), 56% intermediate (1-2), 8% poor (3−5), and 7% missing.

PFS was statistically significantly prolonged among patients receiving bevacizumab compared to placebo; median PFS was 10.2 months vs. 5.4 months [HR 0.60 (95% CI: 0.49, 0.72), p-value <0.0001, stratified log-rank test]. Among the 595 patients with measurable disease, ORR was also significantly higher (30% vs. 12%, p-value <0.0001, stratified CMH test). There was no improvement in OS based on the final analysis conducted after 444 deaths, with a median OS of 23 months in the patients receiving bevacizumab with interferon alfa and 21 months in patients receiving interferon alone [HR 0.86, (95% CI: 0.72, 1.04)]. Results are presented in Figure 4.

Figure 4: Kaplan-Meier Curves for Progression-Free Survival in Metastatic Renal Cell Carcinoma in Study BO17705

14.6 Persistent, Recurrent, or Metastatic Cervical Cancer

Study GOG-0240

The safety and efficacy of bevacizumab were evaluated in patients with persistent, recurrent, or metastatic cervical cancer in a randomized, four-arm, multicenter study comparing bevacizumab with chemotherapy versus chemotherapy alone [GOG-0240 (NCT00803062)]. A total of 452 patients were randomized (1:1:1:1) to receive paclitaxel and cisplatin with or without bevacizumab, or paclitaxel and topotecan with or without bevacizumab.

The dosing regimens for bevacizumab, paclitaxel, cisplatin and topotecan were as follows:

- Day 1: Paclitaxel 135 mg/m^2over 24 hours, Day 2: cisplatin 50 mg/m^2with bevacizumab;
- Day 1: Paclitaxel 175 mg/m^2over 3 hours, Day 2: cisplatin 50 mg/m^2with bevacizumab;
- Day 1: Paclitaxel 175 mg/m^2over 3 hours with cisplatin 50 mg/m^2with bevacizumab;
- Day 1: Paclitaxel 175 mg/m^2over 3 hours with bevacizumab, Days 1-3: topotecan IV 0.75 mg/m^2over 30 minutes

Patients were treated until disease progression or unacceptable adverse reactions. The main outcome measure was OS. Secondary outcome measures included ORR.

The median age was 48 years (20 to 85 years). Of the 452 patients randomized at baseline, 78% of patients were White, 80% had received prior radiation, 74% had received prior chemotherapy concurrent with radiation, and 32% had a platinum-free interval (PFI) of less than 6 months. Patients had a GOG performance status of 0 (58%) or 1 (42%). Demographic and disease characteristics were balanced across arms.

Results are presented in Figure 5 and Table 8.

Figure 5: Kaplan-Meier Curves for Overall Survival in Persistent, Recurrent, or Metastatic Cervical Cancer in Study GOG-0240

Table 8: Efficacy Results in Study GOG-0240

Efficacy Parameter | Bevacizumab with Chemotherapy; (N=227) | Chemotherapy; (N=225)
Overall Survival
Median, in monthsa | 16.8 | 12.9
Hazard ratio (95% CI) | 0.74 (0.58, 0.94)
p-valueb | 0.0132

aKaplan-Meier estimates.

blog-rank test (stratified).

The ORR was higher in patients who received bevacizumab with chemotherapy [45% (95% CI: 39, 52)] compared to patients who received chemotherapy alone [34% (95% CI: 28,40)].

Table 9: Efficacy Results in Study GOG-0240

Efficacy Parameter | Topotecan and Paclitaxel with or without bevacizumab; (N=223) | Cisplatin and Paclitaxel with or without bevacizumab; (N=229)
Overall Survival
Median, in monthsa | 13.3 | 15.5
Hazard ratio (95% CI) | 1.15 (0.91, 1.46)
p-value | 0.23

aKaplan-Meier estimates.

The HR for OS with bevacizumab with cisplatin and paclitaxel as compared to cisplatin and paclitaxel alone was 0.72 (95% CI: 0.51,1.02). The HR for OS with bevacizumab with topotecan and paclitaxel as compared to topotecan and paclitaxel alone was 0.76 (95% CI: 0.55, 1.06).

14.7 Platinum-Resistant Recurrent Epithelial Ovarian, Fallopian Tube, or Primary Peritoneal Cancer

Study MO22224

The safety and efficacy of bevacizumab were evaluated in a multicenter, open-label, randomized study [MO22224 (NCT00976911)] comparing bevacizumab with chemotherapy versus chemotherapyalone in patients with platinum-resistant, recurrent epithelial ovarian, fallopian tube, or primary peritoneal cancer that recurred within <6 months from the most recent platinum-based therapy (N=361). Patients had received no more than 2 prior chemotherapy regimens. Patients received one of the following chemotherapy regimens at the discretion of the investigator: paclitaxel (80 mg/m^2on days 1, 8, 15 and 22 every 4 weeks; pegylated liposomal doxorubicin 40 mg/m^2on day 1 every 4 weeks; or topotecan 4 mg/m^2on days 1, 8 and 15 every 4 weeks or 1.25 mg/m^2on days 1-5 every 3 weeks). Patients were treated until disease progression, unacceptable toxicity, or withdrawal. Forty percent of patients on the chemotherapy alone arm received bevacizumab alone upon progression. The main outcome measure was investigator-assessed PFS. Secondary outcome measures were ORR and OS.

The median age was 61 years (25 to 84 years) and 37% of patients were ≥65 years. Seventy-nine percent had measurable disease at baseline, 87% had baseline CA-125 levels ≥2 times ULN and 31% had ascites at baseline. Seventy-three percent had a PFI of 3 months to 6 months and 27% had PFI of <3 months. ECOG performance status was 0 for 59%, 1 for 34% and 2 for 7% of the patients.

The addition of bevacizumab to chemotherapy demonstrated a statistically significant improvement in investigator-assessed PFS, which was supported by a retrospective independent review analysis. Results for the ITT population are presented in Table 10 and Figure 6. Results for the separate chemotherapy cohorts are presented in Table 11.

Table 10: Efficacy Results in Study MO22224

Efficacy Parameter | Bevacizumab with Chemotherapy (N=179) | Chemotherapy; (N=182)
Progression-Free Survival per Investigator
Median (95% CI), in months | 6.8 (5.6, 7.8) | 3.4 (2.1, 3.8)
HR (95% CI)a | 0.38 (0.30, 0.49)
p-valueb | <0.0001
Overall Survival
Median (95% CI), in months | 16.6 (13.7, 19.0) | 13.3 (11.9, 16.4)
HR (95% CI)a | 0.89 (0.69, 1.14)
Overall Response Rate
Number of Patients with; Measurable Disease at Baseline | 142 | 144
Rate, % (95% CI) | 28% (21%, 36%) | 13% (7%, 18%)
Duration of Response
Median, in months | 9.4 | 5.4

aper stratified Cox proportional hazards model

bper stratified log-rank test

Figure 6: Kaplan-Meier Curves for Investigator-Assessed Progression-Free Survival in Platinum- Resistant Recurrent Epithelial Ovarian, Fallopian Tube, or Primary Peritoneal Cancer in Study MO22224

Table 11: Efficacy Results in Study MO22224 by Chemotherapy

Efficacy Parameter | Paclitaxel |  |  | Topotecan |  | Pegylated Liposomal Doxorubicin
Efficacy Parameter | Bevacizumab with Chemotherapy; (N=60) |  | Chemotherapy (N=55) | Bevacizumab with Chemotherapy (N=57) | Chemotherapy; (N=63) | Bevacizumab with Chemotherapy (N=62) | Chemotherapy; (N=64)
Progression-Free Survival per Investigator
Median, in months (95% CI) | 9.6; (7.8, 11.5) |  | 3.9; (3.5, 5.5) | 6.2; (5.3, 7.6) | 2.1; (1.9, 2.3) | 5.1; (3.9, 6.3) | 3.5; (1.9, 3.9)
Hazard ratioa(95% CI) | 0.47; (0.31, 0.72) |  |  | 0.24; (0.15, 0.38) |  | 0.47; (0.32, 0.71)
Overall Survival
Median, in months (95% CI) | 22.4; (16.7, 26.7) |  | 13.2; (8.2, 19.7) | 13.8; (11.0, 18.3) | 13.3; (10.4, 18.3) | 13.7; (11.0, 18.3) | 14.1; (9.9, 17.8)
Hazard ratioa(95% CI) | 0.64; (0.41, 1.01) |  |  | 1.12; (0.73, 1.73) |  | 0.94; (0.63, 1.42)
Overall Response Rate
Number of patients with measurable disease at baseline | 45 | 43 |  | 46 | 50 | 51 | 51
Rate, % (95% CI) | 53; (39, 68) | 30; (17, 44) |  | 17; (6, 28) | 2; (0, 6) | 16; (6, 26) | 8; (0, 15)
Duration of Response
Median, in months | 11.6 | 6.8 |  | 5.2 | NE | 8.0 | 4.6

aper stratified Cox proportional hazards model

NE=Not Estimable

16 HOW SUPPLIED/STORAGE AND HANDLING

Avzivi (bevacizumab-tnjn) injection is a clear to slightly opalescent, colorless to pale brown, sterile solution for intravenous infusion supplied as single-dose vials in the following strengths:

- 100 mg/4 mL (25 mg/mL): carton of one vial (NDC 82143-001-01)
- 400 mg/16 mL (25 mg/mL) : carton of one vial (NDC 82143-002-01)

Store refrigerated at 2oC to 8oC (36oF to 46oF) in the original carton until time of use to protect from light. Do not freeze or shake the vial or carton.

17 PATIENT COUNSELING INFORMATION

Gastrointestinal Perforations and Fistulae: bevacizumab products may increase the risk of developing gastrointestinal perforations and fistulae. Advise patients to immediately contact their health care provider for high fever, rigors, persistent or severe abdominal pain, severe constipation, or vomiting [see Warnings and Precautions (5.1)].

Surgery and Wound Healing Complications: bevacizumab products can increase the risk of wound healing complications. Instruct patients not to undergo surgery without first discussing this potential risk with their health care provider [see Warnings and Precautions (5.2)] .

Hemorrhage: bevacizumab products can increase the risk of hemorrhage. Advise patients to immediately contact their health care provider for signs and symptoms of serious or unusual bleeding including coughing or spitting blood [see Warnings and Precautions (5.3)] .

Arterial and Venous Thromboembolic Events: bevacizumab products increase the risk of arterial and venous thromboembolic events. Advise patients to immediately contact their health care provider for signs and symptoms of arterial or venous thromboembolism [see Warnings and Precautions (5.4, 5.5)] .

Hypertension: bevacizumab products can increase blood pressure. Advise patients that they will undergo routine blood pressure monitoring and to contact their health care provider if they experience changes in blood pressure [see Warnings and Precautions (5.6)] .

Posterior Reversible Leukoencephalopathy Syndrome: Posterior reversible encephalopathy syndrome (PRES) has been associated with bevacizumab products treatment. Advise patients to immediately contact their health care provider for new onset or worsening neurological function [see Warnings and Precautions (5.7)] .

Renal Injury and Proteinuria: bevacizumab products increase the risk of proteinuria and renal injury, including nephrotic syndrome. Advise patients that treatment with Avzivi requires regular monitoring of renal function and to contact their health care provider for proteinuria or signs and symptoms of nephrotic syndrome [see Warnings and Precautions (5.8)] .

Infusion-Related Reactions: bevacizumab products can cause infusion-related reactions. Advise patients to contact their health care provider immediately for signs or symptoms of infusion-related reactions [see Warnings and Precautions (5.9)].

Congestive Heart Failure: bevacizumab products can increase the risk of developing congestive heart failure. Advise patients to contact their health care provider immediately for signs and symptoms of CHF [see Warnings and Precautions (5.12)].

Embryo-Fetal Toxicity: Advise female patients that bevacizumab products may cause fetal harm and to inform their healthcare provider with a known or suspected pregnancy [see Warnings and Precautions (5.10), Use in Specific Populations (8.1)]. Advise females of reproductive potential to use effective contraception during treatment with Avzivi and for 6 months after the last dose [see Use in Specific Populations (8.3)].

Ovarian Failure: bevacizumab products may lead to ovarian failure. Advise patients of potential options for preservation of ova prior to starting treatment [see Warnings and Precautions (5.11)].

Lactation: Advise women not to breastfeed during treatment with Avzivi and for 6 months after the last dose [see Use in Specific Populations (8.2)]

.

Avzivi® (bevacizumab-tnjn)

Manufactured by:

Bio-Thera Solutions, Ltd.

11 Kaiyuan Boulevard, Huangpu District

Guangzhou, Guangdong Province, China, 510530

U.S. License No. XXXX

Avzivi® is a registered trademark.

©2020 Bio-Thera Solutions, Ltd.

PRINCIPAL DISPLAY PANEL - 4 mL Vial Carton

NDC 82143-001-01

Avzivi®
(bevacizumab-tnjn)
Injection
100 mg/4 mL
(25 mg/mL)

For Intravenous Use.

Single-Dose Vial.
Discard Unused Portion.

Recommended Dosage: See Prescribing Information.
Refrigerate at 2°C to 8°C (36°F to 46°F).
Do not freeze or shake.

Rx only

Bio-Thera
Solutions, Ltd.

US Licence No.: XXXX

PRINCIPAL DISPLAY PANEL - 16 mL Vial Carton

NDC 82143-002-01

Avzivi ®
(bevacizumab-tnjn)
Injection
400 mg/16 mL
(25 mg/mL)

For Intravenous Use.

Single-Dose Vial.
Discard Unused Portion.

Recommended Dosage: See Prescribing Information.
Refrigerate at 2°C to 8°C (36°F to 46°F).
Do not freeze or shake.

Rx only

Bio-Thera
Solutions, Ltd.

US Licence No.: XXXX